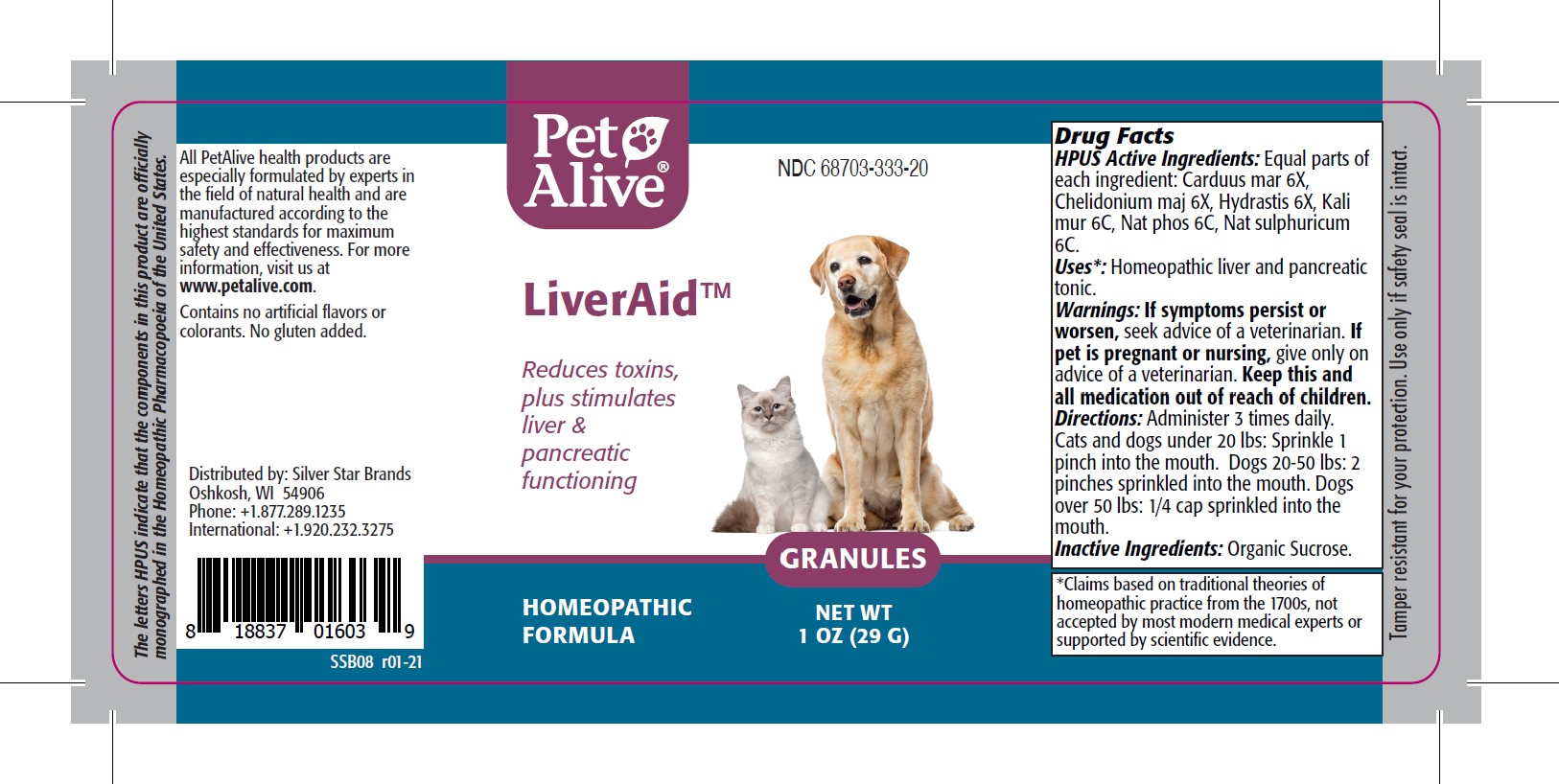 DRUG LABEL: PetAlive LiverAid
NDC: 68703-333 | Form: GRANULE
Manufacturer: SILVER STAR BRANDS
Category: homeopathic | Type: OTC ANIMAL DRUG LABEL
Date: 20251216

ACTIVE INGREDIENTS: SILYBUM MARIANUM SEED 6 [hp_X]/13.33 mg; CHELIDONIUM MAJUS ROOT 6 [hp_X]/13.33 mg; GOLDENSEAL 6 [hp_X]/13.33 mg; POTASSIUM CHLORIDE 6 [hp_C]/13.33 mg; SODIUM PHOSPHATE, DIBASIC, HEPTAHYDRATE 6 [hp_C]/13.33 mg; SODIUM SULFATE 6 [hp_C]/13.33 mg
INACTIVE INGREDIENTS: SUCROSE

PetAlive LiverAid

PURPOSE

Reduces toxins, plus stimulates liver and pancreatic functioning

HPUS Active Ingredients:

Carduus mar 6X
Chelidonium maj 6X
Hydrastis 6X
Kali mur 6C
Nat phos 6C
Nat sulphuricum 6C

INDICATIONS AND USAGE

Uses: Homeopathic liver and pancreatic tonic.

WARNINGS

Warnings: If symptoms persist or worsen, seek advice of a veterinarian

PREGNANCY OR BREAST FEEDING

If pet is pregnant or nursing, give only on advice of a veterinarian.

KEEP OUT OF REACH OF CHILDREN

Keep this and all medication out of reach of children.

INSTRUCTIONS FOR USE

Directions: Administer 3 times daily. Cats and dogs under 20 lbs: Sprinkle 1 pinch into the mouth. Dogs 20-50 lbs: 2 pinches sprinkled into the mouth. Dogs over 50 lbs: 1/4 cap sprinkled into the mouth.

Inactive Ingredients: organic sucrose

INFORMATION FOR OWNERS/CAREGIVERS

The letters HPUS indicate that the components in this product are officially monographed in the Homeopathic Pharmacopoeia of the United States.

All PetAlive health products are especially formulated by experts in the field of natural health and are manufactured according to the highest standards for maximum safety and effectiveness. For more information, visit us at www.petalive.com.

Contains no artificial flavors or colorants. No gluten added.

Distributed by: Silver Star Brands
Oshkosh, WI 54906
Phone: +1.877.289.1235
International: +1.920.232.3275

STORAGE AND HANDLING

Tamper resistant for your protection. Use only if safety seal is intact